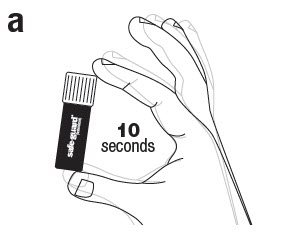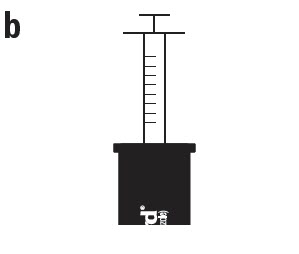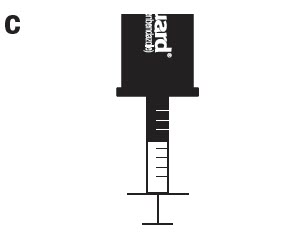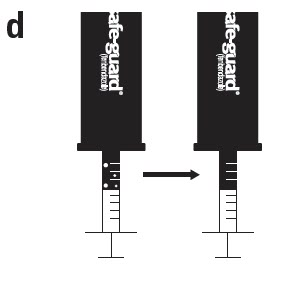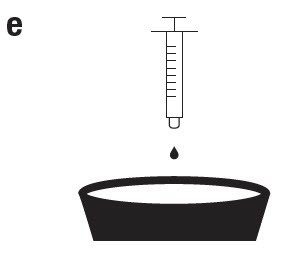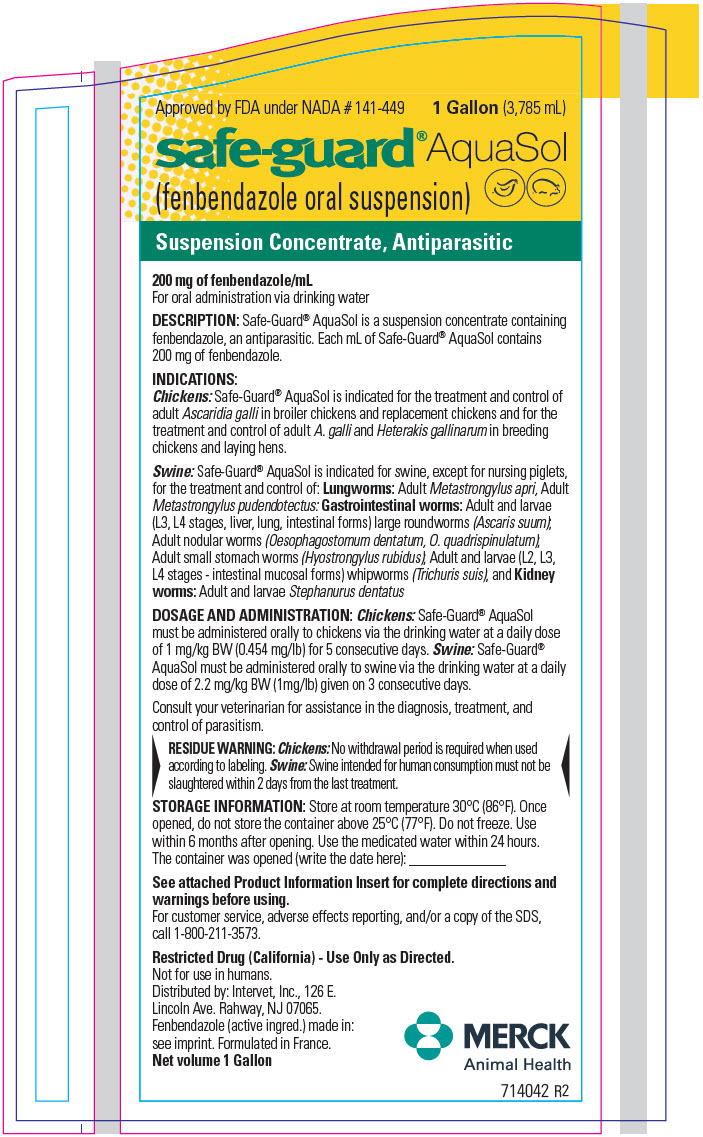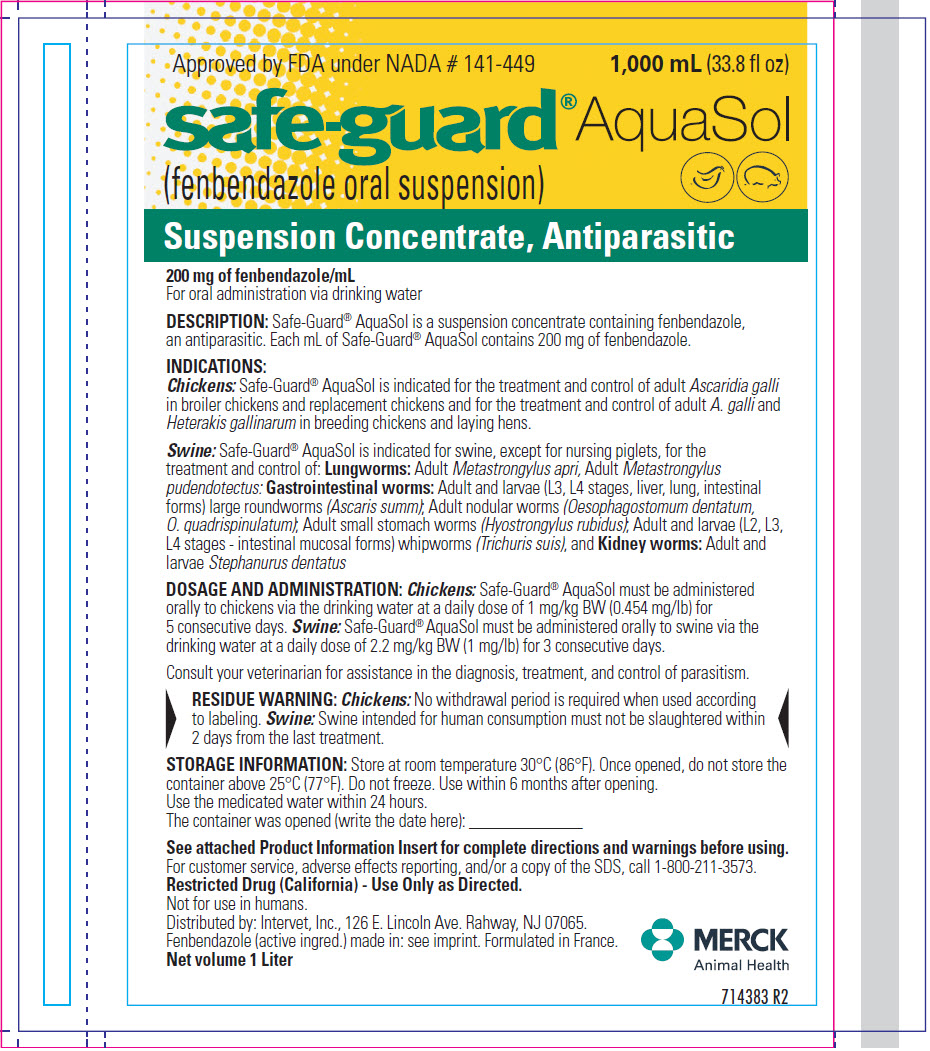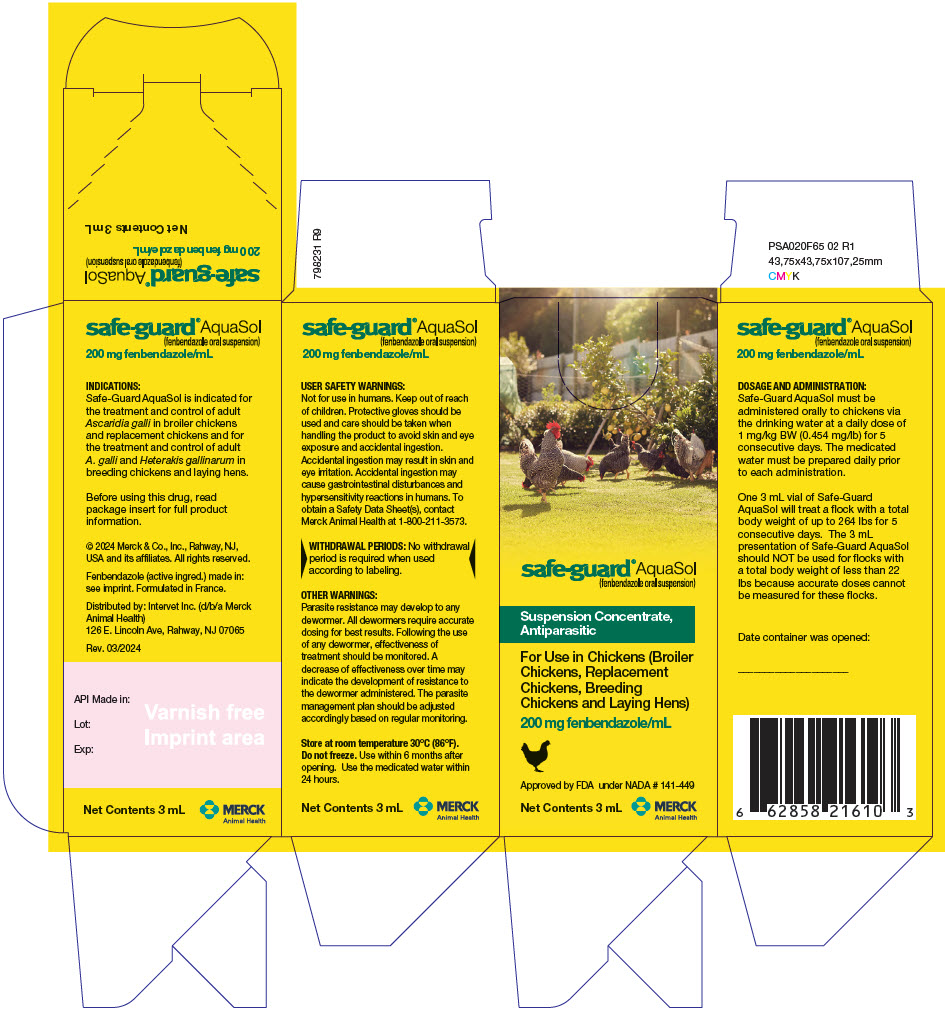 DRUG LABEL: Safe-Guard AquaSol
NDC: 0061-1433 | Form: SUSPENSION
Manufacturer: Merck Sharp & Dohme Corp.
Category: animal | Type: OTC ANIMAL DRUG LABEL
Date: 20241118

ACTIVE INGREDIENTS: FENBENDAZOLE 200 mg/1 mL

Safe-Guard® AquaSol
(fenbendazole oral suspension)

PRODUCT INFORMATION

Approved by FDA under NADA # 141-449

795452 R10
Net Contents 3 mL

safe-guard® AquaSol
(fenbendazole oral suspension)

200 mg fenbendazole/mL

For oral administration via drinking water

DESCRIPTION:

Safe-Guard® AquaSol is a suspension concentrate containing fenbendazole, an antiparasitic. Each mL of Safe-Guard® AquaSol contains 200 mg of fenbendazole.

INDICATIONS:

Safe-Guard® AquaSol is indicated for the treatment and control of adult Ascaridia galli in broiler chickens and replacement chickens and for the treatment and control of adult A. galli and Heterakis gallinarum in breeding chickens and laying hens.

DOSAGE AND ADMINISTRATION:

Safe-Guard® AquaSol must be administered orally to chickens via the drinking water at a daily dose of 1 mg/kg BW (0.454 mg/lb) for 5 consecutive days. The medicated water must be prepared daily prior to each administration. Consult your veterinarian for assistance in the diagnosis, treatment, and control of parasitism.

GENERAL MIXING DIRECTIONS:

Step 1: | Determine the estimated total weight of the entire group of chickens to be treated. One 3mL vial of Safe-Guard® Aquasol will treat a flock with a total body weight of up to 264 lbs for 5 consecutive days. The 3 mL presentation of Safe-Guard® AquaSol should NOT be used for flocks with a total body weight of less than 22 lbs because accurate doses cannot be measured for these flocks.
Step 2: | Consult the table below to determine the volume of water required to prepare the medicated water based on flock weight. Use a clean mixing container appropriate for the daily volume of water, fill with the required amount of water, and set aside.

If the total flock weight is: | Measure the following volume of water: | If the total flock weight is: | Measure the following volume of water:
22 to 55 lbs | 4 cups (0.9 L) | 441 to 550 lbs | 2.5 gal (9.5 L)
56 to 110 lbs | 8 cups (1.9 L) | 551 to 660 lbs | 3 gal (11.4 L)
111 to 220 lbs | 1 gal (3.8 L) | 661 to 770 lbs | 3.5 gal (13.2 L)
221 to 330 lbs | 1.5 gal (5.7 L) | 771 to 880 lbs | 4 gal (15.1 L)
331 to 440 lbs | 2 gal (7.6 L)

Step 3: | Consult the table below to determine the amount of Safe-Guard® AquaSol needed and prepare your medicated water following the mixing instructions below the table.

The table below provides information for one day. The total treatment period is five consecutive days.

 | For each day (for 5 consecutive days)
If the total flock weight is: | Extract the following volume of Safe-Guard® AquaSol from the vial: | And dilute into the following volume of drinking water:
Less than 22 lbs | Not recommended | Not applicable
22 lbs | 0.05 mL | 4 cups (0.9 L)
23 to 33 lbs | 0.075 mL | 4 cups (0.9 L)
34 to 44 lbs | 0.1 mL | 4 cups (0.9 L)
45 to 55 lbs | 0.125 mL | 4 cups (0.9 L)
56 to 66 lbs | 0.15 mL | 8 cups (1.9 L)
67 to 77 lbs | 0.175 mL | 8 cups (1.9 L)
78 to 88 lbs | 0.2 mL | 8 cups (1.9 L)
89 to 99 lbs | 0.225 mL | 8 cups (1.9 L)
100 to 110 lbs | 0.25 mL | 8 cups (1.9 L)
111 to 121 lbs | 0.275 mL | 1 gal (3.7 L)
122 to 132 lbs | 0.3 mL | 1 gal (3.7 L)
133 to 143 lbs | 0.325 mL | 1 gal (3.7 L)
144 to 154 lbs | 0.35 mL | 1 gal (3.7 L)
155 to 165 lbs | 0.375 mL | 1 gal (3.7 L)
166 to 176 lbs | 0.4 mL | 1 gal (3.7 L)
177 to 187 lbs | 0.425 mL | 1 gal (3.7 L)
188 to 198 lbs | 0.45 mL | 1 gal (3.7 L)
199 to 209 lbs | 0.475 mL | 1 gal (3.7 L)
210 to 220 lbs | 0.5 mL | 1 gal (3.7 L)
221 to 231 lbs | 0.525 mL | 1.5 gal (5.6 L)
232 to 242 lbs | 0.55 mL | 1.5 gal (5.6 L)
243 to 253 lbs | 0.575 mL | 1.5 gal (5.6 L)
254 to 264 lbs | 0.6 mL | 1.5 gal (5.6 L)
265 to 275 lbs | 0.625 mL | 1.5 gal (5.6 L)
276 to 286 lbs | 0.65 mL | 1.5 gal (5.6 L)
287 to 297 lbs | 0.675 mL | 1.5 gal (5.6 L)
298 to 308 lbs | 0.7 mL | 1.5 gal (5.6 L)
309 to 319 lbs | 0.725 mL | 1.5 gal (5.6 L)
320 to 330 lbs | 0.75 mL | 1.5 gal (5.6 L)
331 to 341 lbs | 0.775 mL | 2 gal (7.5 L)
342 to 352 lbs | 0.8 mL | 2 gal (7.5 L)
353 to 363 lbs | 0.825 mL | 2 gal (7.5 L)
364 to 374 lbs | 0.85 mL | 2 gal (7.5 L)
375 to 385 lbs | 0.875 mL | 2 gal (7.5 L)
386 to 396 lbs | 0.9 mL | 2 gal (7.5 L)
397 to 407 lbs | 0.925 mL | 2 gal (7.5 L)
408 to 418 lbs | 0.95 mL | 2 gal (7.5 L)
419 to 429 lbs | 0.975 mL | 2 gal (7.5 L)
430 to 440 lbs | 1 mL | 2 gal (7.5 L)
441 to 451 lbs | 1.05 mL | 2.5 gal (9.4 L)
452 to 462 lbs | 1.05 mL | 2.5 gal (9.4 L)
463 to 473 lbs | 1.075 mL | 2.5 gal (9.4 L)
474 to 484 lbs | 1.1 mL | 2.5 gal (9.4 L)
485 to 495 lbs | 1.125 mL | 2.5 gal (9.4 L)
496 to 506 lbs | 1.15 mL | 2.5 gal (9.4 L)
507 to 517 lbs | 1.175 mL | 2.5 gal (9.4 L)
518 to 528 lbs | 1.2 mL | 2.5 gal (9.4 L)
529 to 539 lbs | 1.225 mL | 2.5 gal (9.4 L)
540 to 550 lbs | 1.25 mL | 2.5 gal (9.4 L)
551 to 561 lbs | 1.275 mL | 3 gal (11.3 L)
562 to 572 lbs | 1.3 mL | 3 gal (11.3 L)
573 to 583 lbs | 1.325 mL | 3 gal (11.3 L)
584 to 594 lbs | 1.35 mL | 3 gal (11.3 L)
595 to 605 lbs | 1.375 mL | 3 gal (11.3 L)
606 to 616 lbs | 1.4 mL | 3 gal (11.3 L)
617 to 627 lbs | 1.425 mL | 3 gal (11.3 L)
628 to 638 lbs | 1.45 mL | 3 gal (11.3 L)
639 to 649 lbs | 1.475 mL | 3 gal (11.3 L)
650 to 660 lbs | 1.5 mL | 3 gal (11.3 L)
661 to 671 lbs | 1.525 mL | 3.5 gal (13.2 L)
672 to 682 lbs | 1.55 mL | 3.5 gal (13.2 L)
683 to 693 lbs | 1.575 mL | 3.5 gal (13.2 L)
694 to 704 lbs | 1.6 mL | 3.5 gal (13.2 L)
705 to 715 lbs | 1.625 mL | 3.5 gal (13.2 L)
716 to 726 lbs | 1.65 mL | 3.5 gal (13.2 L)
727 to 737 lbs | 1.675 mL | 3.5 gal (13.2 L)
738 to 748 lbs | 1.7 mL | 3.5 gal (13.2 L)
749 to 759 lbs | 1.725 mL | 3.5 gal (13.2 L)
760 to 770 lbs | 1.75 mL | 3.5 gal (13.2 L)
771 to 781 lbs | 1.775 mL | 4 gal (15.1 L)
782 to 792 lbs | 1.8 mL | 4 gal (15.1 L)
793 to 803 lbs | 1.825 mL | 4 gal (15.1 L)
804 to 814 lbs | 1.85 mL | 4 gal (15.1 L)
815 to 825 lbs | 1.875 mL | 4 gal (15.1 L)
826 to 836 lbs | 1.9 mL | 4 gal (15.1 L)
837 to 847 lbs | 1.925 mL | 4 gal (15.1 L)
848 to 858 lbs | 1.95 mL | 4 gal (15.1 L)
859 to 869 lbs | 1.975 mL | 4 gal (15.1 L)
870 to 880 lbs | 2 mL | 4 gal (15.1 L)

Agitate the vial containing Safe-Guard® AquaSol (fenbendazole oral suspension) for approximately 10 seconds.

Attach the provided syringe to the vial cap while keeping the container upright. Use only the syringe supplied by Merck Animal Health for the preparation of the medicated water.

Leave the syringe attached to the vial and turn both upside down. Hold the syringe and vial firmly in one hand. With your free hand, pull the plunger to withdraw the correct amount of Safe-Guard® AquaSol into the syringe. Before you remove the syringe out of the vial, check the syringe for air bubbles. If there are air bubbles in the syringe, proceed to Step d. If there are no air bubbles in the syringe, proceed to Step e.

If bubbles are in the syringe, hold the syringe and vial upside down and tap the side of the syringe until the bubbles float to the top. Push the bubbles out with the plunger back into the vial. If needed, draw more Safe-Guard® AquaSol until you have the correct dose. Confirm that there are no air bubbles in the syringe before proceeding to Step e.

Detach the syringe from the cap and fully dispense its contents into the mixing container that contains the measured volume of drinking water. Do not submerge or allow the syringe to come in contact with the water. Mix well by stirring until the medicated water appears uniformly hazy.

Each treatment day, empty all the flocks' waterers before adding the medicated water. Provide this medicated water to your birds first thing in the morning, when it is peak of consumption. If you have more than one waterer, distribute the total volume of medicated water in equal parts among the waterers. During treatment, all birds must have unrestricted access to the medicated water, and no access to other sources of water. After complete consumption of the medicated water, the animals should have access to non-medicated drinking water ad libitum. Ensure that the total amount of medicated water offered is consumed.

CLEANING INSTRUCTIONS FOR DOSING SYRINGE:

a: Do not discard the syringe as it will be needed for next treatment. The provided syringe can be reused. Perform maintenance in a clean, sanitary work area free from potential contaminants, and discard all water used to clean the syringe as waste.
b: Clean all external debris off the syringe with hot tap water.
c: Rinse the syringe in clean tap water by pulling and pushing the plunger a few times before disassembling the syringe.
d: Disassemble the syringe, which includes the syringe barrel and the plastic plunger, and clean with hot tap water.
  i. When you disassemble the syringe to clean it, check that the syringe has worked properly.
    If product has accumulated in the syringe barrel or on the plastic plunger, discard the syringe and use a new syringe.
  ii. If the plastic plunger sticks when inserted back into the syringe barrel, discard the syringe and use a new syringe.
    Do not use lubricant on the plastic plunger to reduce sticking.
    To obtain replacement syringes, contact Merck Animal Health Customer Care at 1-800-521-5767.
e: Reassemble the syringe once all parts of the syringe are dry.
f: Store the syringe in a clean, dry location.

USER SAFETY WARNINGS:

Not for use in humans. Keep out of reach of children. Protective gloves should be used and care should be taken when handling the product to avoid skin and eye exposure and accidental ingestion. Accidental exposure may result in skin and eye irritation. Accidental ingestion may cause gastrointestinal disturbances and hypersensitivity reactions in humans. Safety Data Sheets (SDS's) can be found at https://www.msd.com/research/safety-data-sheets/# or by calling 1-800-521-5767.

WITHDRAWAL PERIODS:

No withdrawal period is required when used according to labeling.

OTHER WARNINGS:

Parasite resistance may develop to any dewormer. All dewormers require accurate dosing for best results. Following the use of any dewormer, effectiveness of treatment should be monitored. A decrease of effectiveness over time may indicate the development of resistance to the dewormer administered. The parasite management plan should be adjusted accordingly based on regular monitoring.

EFFECTIVENESS:

Six pivotal dose confirmation studies and five field effectiveness studies were conducted to evaluate the effectiveness of Safe-Guard® AquaSol oral suspension against adult A. galli in broiler chickens and replacement chickens and against A. galli and H. gallinarum in breeding chickens and laying hens. Safe-Guard® AquaSol was administered orally in drinking water at 1 mg fenbendazole/kg body weight/day for 5 consecutive days. The chickens were necropsied 7 to 8 days after the last treatment, and adult worms in the intestines and ceca of the chickens in the control and treated groups were counted to determine percent efficacy.

Three dose confirmation studies were conducted in European Union (EU), using 105 Rhode Island Red breed hens (2 years old) for each study. In all three studies, the efficacy against A. galli (97.9%, 97.3%, and 93.9%) and H. gallinarum (99.8%, 96.9%, and 97.3%) was greater than 90%. A fourth dose confirmation study was conducted in the United States (US) using 264 Rhode Island Red breed hens (12 months old). In the study, the efficacy against adult A. galli and H. gallinarum was 98.7% and 99.2%, respectively. A fifth dose confirmation study was conducted in the US using 176 Cobb breed broiler chickens (4 to 5 weeks old). In the study, the efficacy against adult A. galli was 99.4%.

A sixth dose confirmation study was conducted in the US using 176 Ross breed broiler chickens (4 to 5 weeks old). In the study, the efficacy against adult A. galli was 100%.

A field effectiveness study was conducted in the EU in a flock of 13,244 Hy-Line layer breed replacement chickens (13 weeks old). Fifteen chickens were necropsied before treatment initiation, and 15 chickens were necropsied seven days after treatment for worm counts. The efficacy against adult A. galli was 90.2%. A second field effectiveness study was conducted in the US using 550 Ross breed broiler chickens (4 to 5 weeks old). The efficacy against adult A. galli was 100%. A third field effectiveness study was conducted in the US using 550White Leghorn replacement chickens (14 weeks old). The efficacy against adult A. galli and H. gallinarum was 100% and 88.9%, respectively. A fourth field effectiveness study was conducted in the US using 550 Cobb breed breeder hens (63 weeks old). The efficacy against adult A. galli and H. gallinarum was 97.6% and 95.3%, respectively. A fifth effectiveness study was conducted in the US using 550 Cobb breed broiler chickens (4 to 5 weeks old). The efficacy against adult A. galli was 100%.

The pivotal dose confirmation studies and field effectiveness studies demonstrated substantial evidence of effectiveness of Safe-Guard® AquaSol at the dose of 1 mg fenbendazole/kg body weight/day for 5 consecutive days against adult A. galli in broiler chickens and replacement chickens and against adult A. galli and H. gallinarum in breeding chickens and laying hens.

ANIMAL SAFETY:

Two margin of safety studies (growing broiler chickens and laying hens at peak egg production) and one reproductive safety study (broiler breeder chickens) were conducted. These studies supported the safety of Safe-Guard® AquaSol in broiler chickens, replacement chickens, laying hens and breeding chickens when administered in drinking water at 1 mg fenbendazole/kg body weight/ day for 5 consecutive days.

The margin of safety in broiler chickens was conducted in 480 broiler chickens. Safe-Guard® AquaSol was administered orally as medicated drinking water to three groups of 120 chickens (60 male and 60 female in each group) at 1, 3, and 5 mg fenbendazole/kg body weight/day (1, 3, and 5 times the recommended label dose) for 15 consecutive days (3 times the recommended duration). Another group of 120 chickens (60 male and 60 female) was provided non-medicated drinking water and used as a control group. In all chickens, feed and water intake, body weights, clinical health, and mortality were recorded. Hematology and clinical chemistry parameters were evaluated in 24 chickens from each group. At the end of the treatment phase, gross necropsies were performed on 48 chickens from each group, and organs weights were evaluated. Histopathologic examinations were performed on 48 chickens each from the control and 5 mg fenbendazole/kg body weight groups. No clinically significant effects related to the administration of Safe-Guard® AquaSol were observed for any of the parameters evaluated.

The margin of safety in laying hens was conducted in 144 laying hens. Safe-Guard® AquaSol was administered orally as medicated drinking water to three groups of 36 hens at 1, 3, and 5 times the recommended label dose (1, 3, and 5 mg fenbendazole/kg body weight/day) for 15 consecutive days (3 times the recommended duration). Another group of 36 hens was provided non-medicated drinking water and used as control group. In all hens, feed and water intake, body weights, clinical health, mortality, egg production, and egg quality parameters (including egg shell thickness and strength, egg weight, and Haugh unit) were evaluated. Hematology and clinical chemistry parameters were evaluated in 12 hens from each group.

At the end of the treatment phase, gross necropsies were performed on 12 hens from each group, and organs weights were evaluated. Histopathologic examinations were performed on 12 hens each from the control and 5 mg fenbendazole/kg body weight groups. No clinically significant effects related to the administration of Safe-Guard® AquaSol were observed for any of the parameters evaluated.

The reproductive safety in broiler breeding chickens was conducted in 220 broiler breeder chickens.

Safe-Guard® AquaSol was administered orally as medicated drinking water to a group of 110 breeding chickens (10 male and 100 female) at 3 mg fenbendazole/kg body weight/day (3 times the recommended label dose) for 21 consecutive days (4 times the recommended duration). Another group of 110 breeding chickens (10 male and 100 female) were provided non-medicated drinking water and used as a control group. The parameters evaluated in the study included feed and water intake, body weights, clinical health, egg production and weight, fertility, hatchability, and 14-day old chick viability. Necropsy of unhatched eggs was performed to record the percentage of dead embryos and dead and culled hatchlings. At the end of the treatment phase, 30 breeding chickens (10 male and 20 female) from each group were necropsied; and gross pathology and weights of testes and female reproductive tracts were evaluated. Histopathologic evaluations were performed on the gross lesions collected during the necropsy. No clinically significant effects related to the administration of Safe-Guard® AquaSol were observed for any of the parameters evaluated.

QUESTIONS/COMMENTS?

For technical information or to report a suspected adverse event, please contact Merck Animal Health at 1-800-211-3573 or www.merck-animal-health-usa.com. For additional information about adverse drug experience reporting for animal drugs, contact FDA at 1-888-FDA-VETS, or http://www.fda.gov/reportanimalae

STORAGE INFORMATION:

Store at room temperature 30°C (86°F). Do not freeze.

Use within 6 months after opening. Use the medicated water within 24 hours.

HOW SUPPLIED:

3 mL in glass vial.

FOR PATENT INFORMATION:

http://www.merck.com/product/patent/home.html.

USE ONLY AS DIRECTED

Copyright © 2024 Merck & Co., Inc., Rahway, NJ, USA and its affiliates.

All rights reserved.

Formulated in France.

DISTRIBUTED BY:

Intervet Inc. (d/b/a Merck Animal Health), Rahway, NJ USA 07065

Approved by FDA under NADA # 141-449

Rev. 03/2024

PRINCIPAL DISPLAY PANEL - 3,785 mL Container Label

Approved by FDA under NADA # 141-449
1 Gallon (3,785 mL)

safe-guard® AquaSol
(fenbendazole oral suspension)

Suspension Concentrate, Antiparasitic

200 mg of fenbendazole/mL
For oral administration via drinking water

DESCRIPTION: Safe-Guard® AquaSol is a suspension concentrate containing
fenbendazole, an antiparasitic. Each mL of Safe-Guard® AquaSol contains
200 mg of fenbendazole.

INDICATIONS:
Chickens: Safe-Guard® AquaSol is indicated for the treatment and control of
adult Ascaridia galli in broiler chickens and replacement chickens and for the
treatment and control of adult A. galli and Heterakis gallinarum in breeding
chickens and laying hens.

Swine: Safe-Guard® AquaSol is indicated for swine, except for nursing piglets,
for the treatment and control of: Lungworms: Adult Metastrongylus apri, Adult
Metastrongylus pudendotectus: Gastrointestinal worms: Adult and larvae
(L3, L4 stages, liver, lung, intestinal forms) large roundworms (Ascaris suum);
Adult nodular worms (Oesophagostomum dentatum, O. quadrispinulatum);
Adult small stomach worms (Hyostrongylus rubidus); Adult and larvae (L2, L3,
L4 stages - intestinal mucosal forms) whipworms (Trichuris suis), and Kidney
worms: Adult and larvae Stephanurus dentatus

DOSAGE AND ADMINISTRATION: Chickens: Safe-Guard® AquaSol
must be administered orally to chickens via the drinking water at a daily dose
of 1 mg/kg BW (0.454 mg/lb) for 5 consecutive days. Swine: Safe-Guard®
AquaSol must be administered orally to swine via the drinking water at a daily
dose of 2.2 mg/kg BW (1mg/lb) given on 3 consecutive days.

Consult your veterinarian for assistance in the diagnosis, treatment, and
control of parasitism.

RESIDUE WARNING: Chickens: No withdrawal period is required when used
according to labeling. Swine: Swine intended for human consumption must not be
slaughtered within 2 days from the last treatment.

STORAGE INFORMATION: Store at room temperature 30°C (86°F). Once
opened, do not store the container above 25°C (77°F). Do not freeze. Use
within 6 months after opening. Use the medicated water within 24 hours.
The container was opened (write the date here): _____________

See attached Product Information Insert for complete directions and
warnings before using.

For customer service, adverse effects reporting, and/or a copy of the SDS,
call 1-800-211-3573.

Restricted Drug (California) - Use Only as Directed.

Not for use in humans.
Distributed by: Intervet, Inc., 126 E.
Lincoln Ave. Rahway, NJ 07065.
Fenbendazole (active ingred.) made in:
see imprint. Formulated in France.

Net volume 1 Gallon

MERCK
Animal Health
714042 R2

PRINCIPAL DISPLAY PANEL - 1,000 mL Container Label

Approved by FDA under NADA # 141-449
1,000 mL (33.8 fl oz)

safe-guard® AquaSol
(fenbendazole oral suspension)

Suspension Concentrate, Antiparasitic

200 mg of fenbendazole/mL
For oral administration via drinking water

DESCRIPTION: Safe-Guard® AquaSol is a suspension concentrate containing fenbendazole,
an antiparasitic. Each mL of Safe-Guard® AquaSol contains 200 mg of fenbendazole.

INDICATIONS:
Chickens: Safe-Guard® AquaSol is indicated for the treatment and control of adult Ascaridia galli
in broiler chickens and replacement chickens and for the treatment and control of adult A. galli and
Heterakis gallinarum in breeding chickens and laying hens.

Swine: Safe-Guard® AquaSol is indicated for swine, except for nursing piglets, for the
treatment and control of: Lungworms: Adult Metastrongylus apri, Adult Metastrongylus
pudendotectus: Gastrointestinal worms: Adult and larvae (L3, L4 stages, liver, lung, intestinal
forms) large roundworms (Ascaris summ); Adult nodular worms (Oesophagostomum dentatum,
O. quadrispinulatum); Adult small stomach worms (Hyostrongylus rubidus); Adult and larvae (L2, L3,
L4 stages - intestinal mucosal forms) whipworms (Trichuris suis), and Kidney worms: Adult and
larvae Stephanurus dentatus

DOSAGE AND ADMINISTRATION: Chickens: Safe-Guard® AquaSol must be administered
orally to chickens via the drinking water at a daily dose of 1 mg/kg BW (0.454 mg/lb) for
5 consecutive days. Swine: Safe-Guard® AquaSol must be administered orally to swine via the
drinking water at a daily dose of 2.2 mg/kg BW (1 mg/lb) for 3 consecutive days.

Consult your veterinarian for assistance in the diagnosis, treatment, and control of parasitism.

RESIDUE WARNING: Chickens: No withdrawal period is required when used according
to labeling. Swine: Swine intended for human consumption must not be slaughtered within
2 days from the last treatment.

STORAGE INFORMATION: Store at room temperature 30°C (86°F). Once opened, do not store the
container above 25°C (77°F). Do not freeze. Use within 6 months after opening.
Use the medicated water within 24 hours.
The container was opened (write the date here): _________________

See attached Product Information Insert for complete directions and warnings before using.
For customer service, adverse effects reporting, and/or a copy of the SDS, call 1-800-211-3573.

Restricted Drug (California) - Use Only as Directed.

Not for use in humans.
Distributed by: Intervet, Inc., 126 E. Lincoln Ave. Rahway, NJ 07065.
Fenbendazole (active ingred.) made in: see imprint. Formulated in France.
Net volume 1 Liter

MERCK
Animal Health
714383 R2

PRINCIPAL DISPLAY PANEL - 3 mL Bottle Carton

safe-guard® AquaSol
(fenbendazole oral suspension)

Suspension Concentrate,
Antiparasitic

For Use in Chickens (Broiler
Chickens, Replacement
Chickens, Breeding
Chickens and Laying Hens)

200 mg fenbendazole/mL

Approved by FDA under NADA # 141-449

Net Contents 3 mL

MERCK
Animal Health